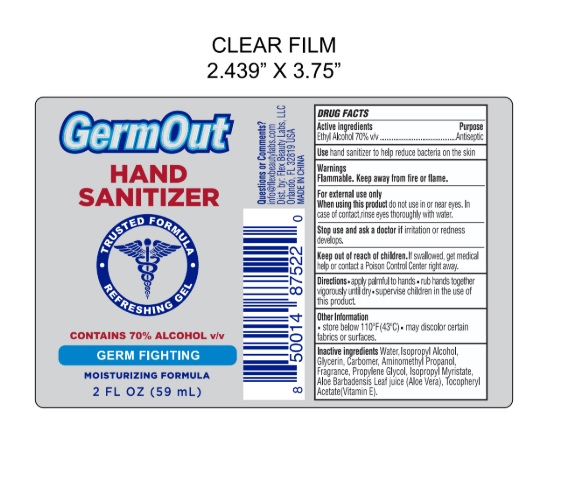 DRUG LABEL: Germ Out Hand Sanitizer
NDC: 72308-007 | Form: GEL
Manufacturer: Flex Beauty Labs
Category: otc | Type: HUMAN OTC DRUG LABEL
Date: 20200609

ACTIVE INGREDIENTS: ALCOHOL 0.7 mL/1 mL
INACTIVE INGREDIENTS: WATER; ISOPROPYL ALCOHOL; ALOE VERA LEAF; PROPYLENE GLYCOL; GLYCERIN; ISOPROPYL MYRISTATE; .ALPHA.-TOCOPHEROL ACETATE, D-; AMINOMETHYLPROPANOL

GERM OUT Hand Sanitizer

Active Ingredients

Ethyl Alcohol 70% v/v.

Purpose: Antiseptic

Purpose

Antiseptic

Use

hand sanitizer to help reduce bacteria on the skin

Safety Instructions

Flammable, Keep away from fire and flame

When usinng this product

do not use in or near eyes. In case of contact, rinse eyes thoroghly with water.

Stop using

Stop use and ask a doctor if irritation or redness develops.

KEEP OUT OF REACH OF CHILDREN

If swallowed, get medical help or contact Poison Control right away

Other Information

Store below 110°F (43°C)
May discolor certain fabrics or surfaces.

Inactive Ingredients

Water (aqua), Isopropyl Alcohol, Glycerin, Carbomer, Aminomethyl Propanol, Fragrance, Propylene Glycol, Isopropyl Myristate, Aloe Barbadensis Leaf Juice (Aloe Vera), Fragrance, Glycerin, Tocopheryl Acetate (Vitamin E)

Directions

- apply palmful to hands.
- rub hands together vigorously until dry.
- supervise children in the use of this product.